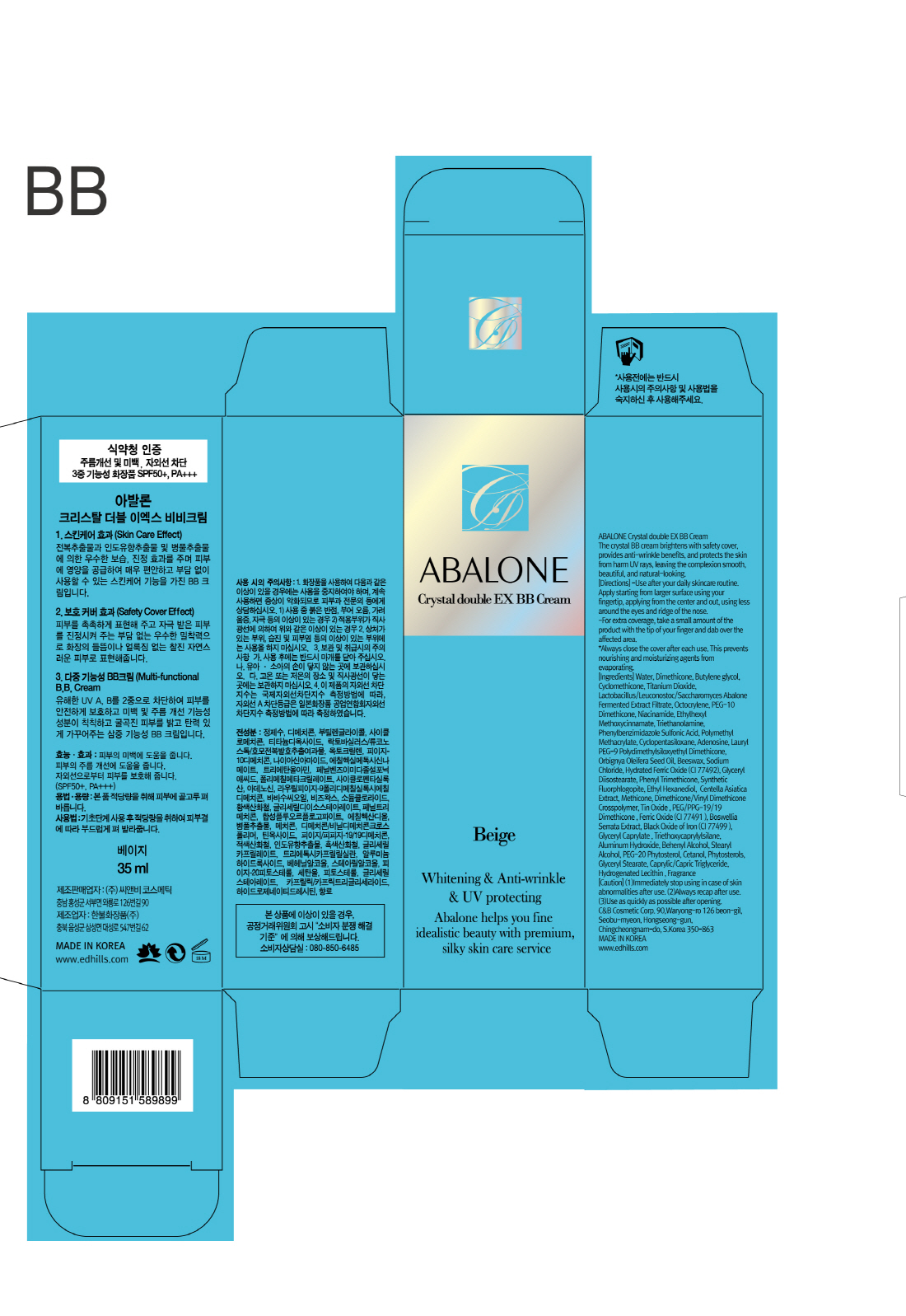 DRUG LABEL: ABALONE CRYSTALDOUBLE EX BB
NDC: 60611-0009 | Form: CREAM
Manufacturer: C&BCOSMETIC Co.,Ltd.
Category: otc | Type: HUMAN OTC DRUG LABEL
Date: 20170310

ACTIVE INGREDIENTS: OCTOCRYLENE 3 g/100 mL; NIACINAMIDE 2 g/100 mL; TITANIUM DIOXIDE 9.9 g/100 mL; ADENOSINE 0.04 g/100 mL; OCTINOXATE 2 g/100 mL
INACTIVE INGREDIENTS: WATER; GLYCERIN; BUTYLENE GLYCOL

Drug Facts

ACTIVE INGREDIENT

Niacinamide, Adenosine, Titanium Dioxide, Ethylhexyl Methoxycinnamate, Octocrylene

INACTIVE INGREDIENT

Water, Butylene Glycol, Etc

PURPOSE

Skin Protectant - Anti-Wrinkle, Whitening, UV Protecting

keep out or reach of the children

INDICATIONS AND USAGE

Use after your daily skincare routine
Apply starting from larger surface using your fingertip, applying from the center and out, using less around the eyes and ridge of the nose
For extra coverage, take a small amount of the product with the tip of your finger and dab over the affected area.
*Always close the cover after each use. This prevents nourishing and moisturizing agents from evaporating.

WARNINGS

1. Do not use in the following cases(Eczema and scalp wounds)
2.Side Effects
1)Due to the use of this druf if rash, irritation, itching and symptopms of hypersnesitivity occur dicontinue use and consult your phamacisr or doctor
3.General Precautions
1)If in contact with the eyes, wash out thoroughty with water If the symptoms are servere, seek medical advice immediately
2)This product is for exeternal use only. Do not use for internal use
4.Storage and handling precautions
1)If possible, avoid direct sunlight and store in cool and area of low humidity
2)In order to maintain the quality of the product and avoid misuse
3)Avoid placing the product near fire and store out in reach of children

DOSAGE AND ADMINISTRATION

for external use only